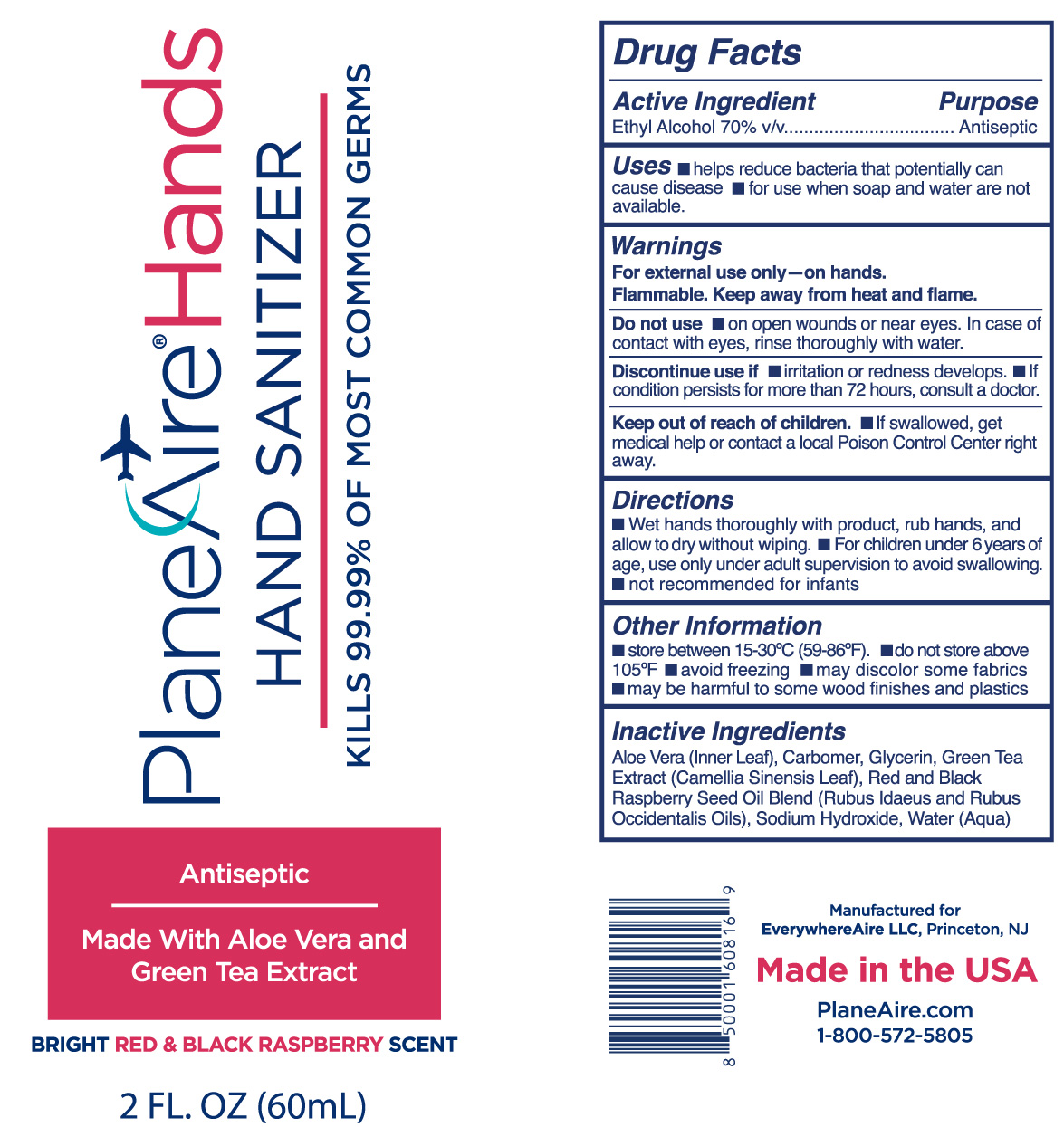 DRUG LABEL: PlaneAire Hands
NDC: 80335-111 | Form: GEL
Manufacturer: EverywhereAire LLC
Category: otc | Type: HUMAN OTC DRUG LABEL
Date: 20210111

ACTIVE INGREDIENTS: ALCOHOL 70 mL/100 mL
INACTIVE INGREDIENTS: ALOE VERA LEAF POLYSACCHARIDES; GLYCERIN; WATER; GREEN TEA LEAF; CARBOMER 980; SODIUM HYDROXIDE; BLACK RASPBERRY; RASPBERRY SEED OIL

PlaneAire Hands gel Black Raspberry and Red Raspberry hand sanitizer

Active Ingredient(s)

Ethyl alcohol 70% v/v.

Purpose

Antiseptic

Use

Hand Sanitizer to help reduce bacteria that potentially can cause disease. For use when soap and water are not available.

Warnings

For external use only- on hands. Flammable. Keep away from heat or flame

Do not use

On open skin wounds or near eyes. In case of contact with eyes, rinse thoroughly with water

When using this product keep out of eyes. In case of contact with eyes, rinse eyes thoroughly with water.
Discontinue use if irritation or redness occurs. If condition persists for more than 72 hours, consult a doctor.

STOP USE

Discontinue use if irritatton or redness occurs. If condition persists for more than 72 hours, consult a doctor.

Keep out of reach of children. If swallowed, get medical help or contact a Poison Control Center right away.

Directions

- Wet hands thoroughly with product, rub hands, and allow to dry without wiping
- For children under 6 years of age, use only adult supervision to avoid swallowing
- not recommended for infants

Directions

Wet hands thoroughly with product, rub hands, and allow to dry without wiping
For children under 6 years of age, use only adult supervision to avoid swallowing
not recommended for infants

Other information

- Store between 15-30C (59-86F)
- do not store above 105 F
- may discolor some fabrics
- may be harmful to some wood finishes and plastics

Inactive ingredients

Aloe vera inner leaf, carbomer, glycerin, green tea extract, black raspberry, red raspberry, sodium hydroxide, water

Package Label - Principal Display Panel

60 mL NDC: 80335-111-02